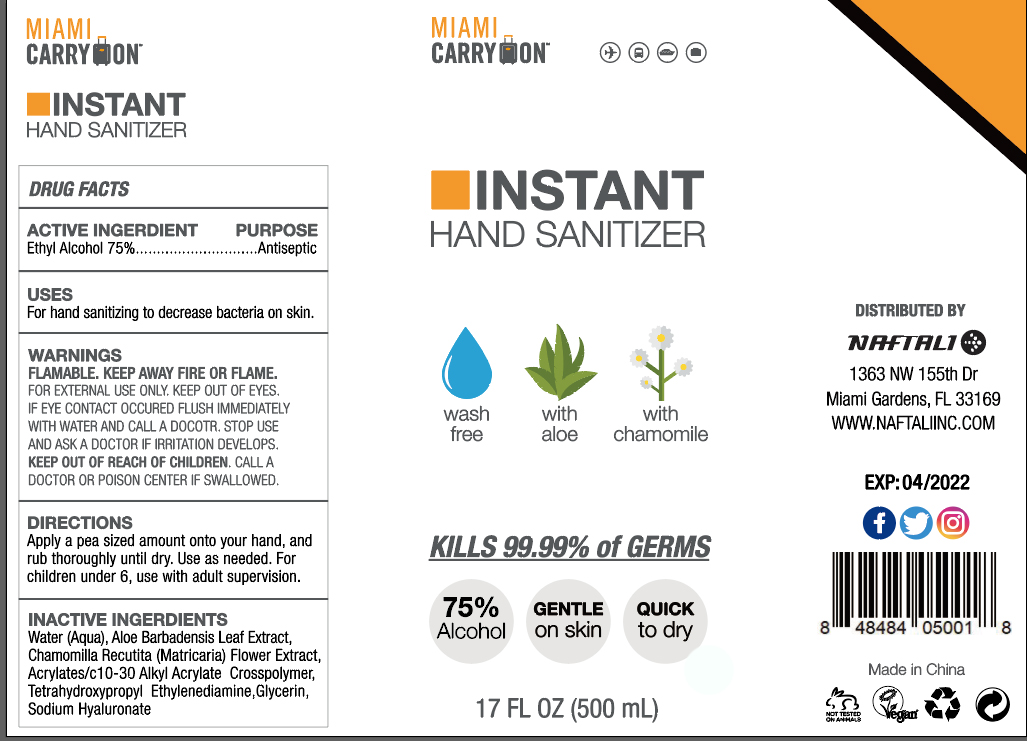 DRUG LABEL: Instant hand sanitizer
NDC: 75819-001 | Form: GEL
Manufacturer: Naftali Inc
Category: otc | Type: HUMAN OTC DRUG LABEL
Date: 20200422

ACTIVE INGREDIENTS: ALCOHOL 75 mL/100 mL
INACTIVE INGREDIENTS: GLYCERIN; ALOE VERA LEAF; EDETOL; WATER; CHAMOMILE; HYALURONATE SODIUM; CARBOMER INTERPOLYMER TYPE A (55000 CPS)

Active Ingredient(s)

Ethyl Alcohol 75% v/v. Purpose: Antiseptic

Purpose

Antiseptic, Hand Sanitizer

USES

For hand sanitizing to decrease bacteria on skin.

WARNINGS

Flammable. Keep away fire or flame.

For external use only. Keep out of eyes. If eye contact occured, flush immediately with water and call a doctor. Stop use and ask a doctor if irritation develops.

KEEP OUT OF REACH OF CHILDREN

Call a doctor or Poison Center if swallowed.

DIRECTIONS

Apply a pea sized amount onto your hand, and rub throughly until dry.

Use as needed. For children under 6, use with adult supervision.

INACTIVE INGREDIENTS

glycerin, hydrogen peroxide, purified water USP

Package Label - Principal Display Panel

500 mL NDC: 75819-001-01